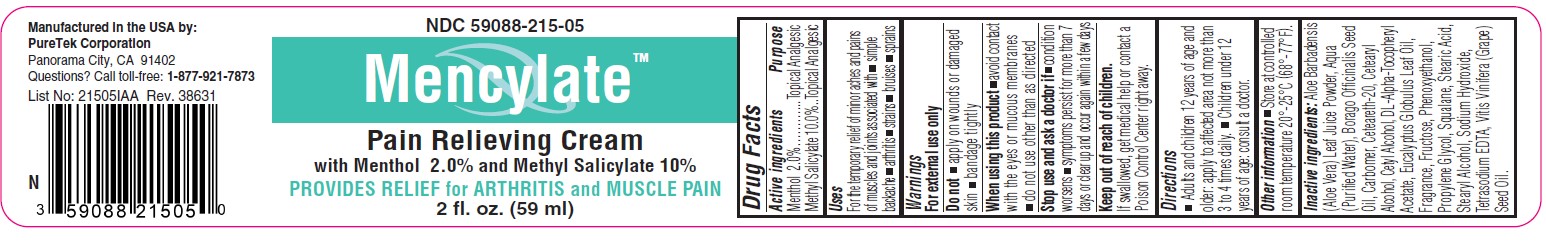 DRUG LABEL: Mencylate
NDC: 59088-215 | Form: CREAM
Manufacturer: PureTek Corporation
Category: otc | Type: HUMAN OTC DRUG LABEL
Date: 20241001

ACTIVE INGREDIENTS: METHYL SALICYLATE 100 mg/1 mL; MENTHOL 20 mg/1 mL
INACTIVE INGREDIENTS: ALOE VERA LEAF; PROPYLENE GLYCOL; BORAGE SEED OIL; CARBOMER 934; POLYOXYL 20 CETOSTEARYL ETHER; CETOSTEARYL ALCOHOL; CETYL ALCOHOL; EUCALYPTUS OIL; FRUCTOSE; PHENOXYETHANOL; WATER; SQUALANE; STEARIC ACID; STEARYL ALCOHOL; EDETATE SODIUM; .ALPHA.-TOCOPHEROL ACETATE, DL-; GRAPE SEED OIL; SODIUM HYDROXIDE

Mencylate

Active ingredients

Menthol 2.0%
Methyl Salicylate 10.0%

Purpose

Topical Analgesic

Uses

For the temporary relief of minor aches and pains of muscles and joints associated with • simple backache • arthritis • strains • bruises • sprains

Warnings

For external use only.

Do not

• apply on wounds or damaged skin • bandage tightly

When using this product

• avoid contact with the eyes or mucous membranes • do not use other than as directed

Stop use and ask a doctor if

• condition worsens • symptoms persist for more than 7 days or clear up and occur again within a few days

Keep out of reach of children.

If swallowed, get medical help or contact a Poison Control Center right away.

Directions

• Adults and children 12 years of age and older: apply to affected area not more than 3 to 4 times daily. • Children under 12 years of age: consult a doctor.

Other information

• Store at controlled room temperature 20°-25°C (68°-77°F).

Inactive ingredients:

Aloe Barbadensis (Aloe Vera) Leaf Juice Powder, Aqua (Purified Water), Borago Officinalis Seed Oil, Carbomer, Ceteareth-20, Cetearyl Alcohol, Cetyl Alcohol, DL-Alpha-Tocopheryl Acetate, Eucalyptus Globulus Leaf Oil, Fragrance, Fructose, Phenoxyethanol, Propylene Glycol, Squalane, Stearic Acid, Stearyl Alcohol, Sodium Hydroxide, Tetrasodium EDTA, Vitis Vinifera (Grape) Seed Oil.

MencylateTM

Manufactured in the USA by:
PureTek Corporation
Panorama City, CA 91402
Questions? Call toll-free: 1-877-921-7873